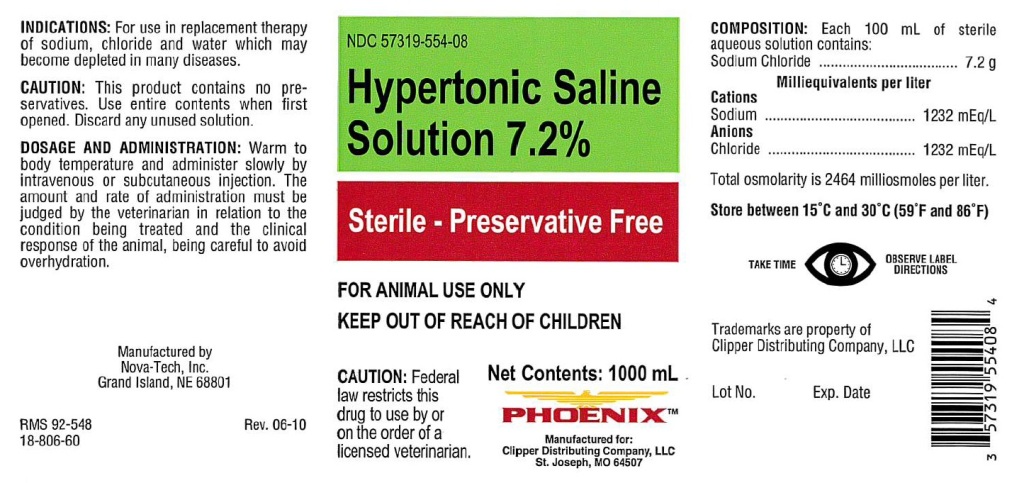 DRUG LABEL: Hypertonic Saline
NDC: 57319-554 | Form: INJECTION, SOLUTION
Manufacturer: Phoenix
Category: animal | Type: PRESCRIPTION ANIMAL DRUG LABEL
Date: 20180129

ACTIVE INGREDIENTS: SODIUM CHLORIDE 7.2 g/100 mL

Hypertonic Saline Solution 7.2%

INDICATIONS:

For use in replacement therapy
of sodium, chloride and water which may
become depleted in many diseases.

CAUTION:

This product contains no pre-
servatives. Use entire contents when first
opened. Discard any unused solution.

DOSAGE AND ADMINISTRATION:

Warm to
body temperature and administer slowly by
intravenous or subcutaneous injection. The
amount and rate of administration must be
judged by the veterinarian in relation to the
condition being treated and the clinical
response of the animal, being careful to avoid
overhydration.

VETERINARY INDICATIONS

FOR ANIMAL USE ONLY

KEEP OUT OF REACH OF CHILDREN

CAUTION:

Federal law restricts this drug to use by or on the order of a licensed veterinarian.

COMPOSITION:

Each 100 mL of sterile
aqueous solution contains:
Sodium Chloride ................... 7.2 g

Milliequivalents per liter

Cations
Sodium ......................... 1232 mEq/L
Anions
Chloride ........................ 1232 mEq/L

Total osmolarity is 2464 milliosmoles per liter.

STORAGE AND HANDLING

Store between 15°C and 30°C (59°F and 86°F)

GENERAL PRECAUTIONS

TAKE TIME OBSERVE LABEL DIRECTIONS

INFORMATION FOR OWNERS/CAREGIVERS

Manufactured by
Nova-Tech, Inc.
Grand Island, NE 68801

RMS 92-548

18-806-60

Rev. 06-10

NDC 57319-554-08

Sterile - Preservative Free

Net Contents: 1000 mL

Manufactured for:
Clipper Distributing Company, LLC
St. Joseph, MO 64507

Trademarks are property of
Clipper Distributing Company, LLC

Lot No.

Exp. Date